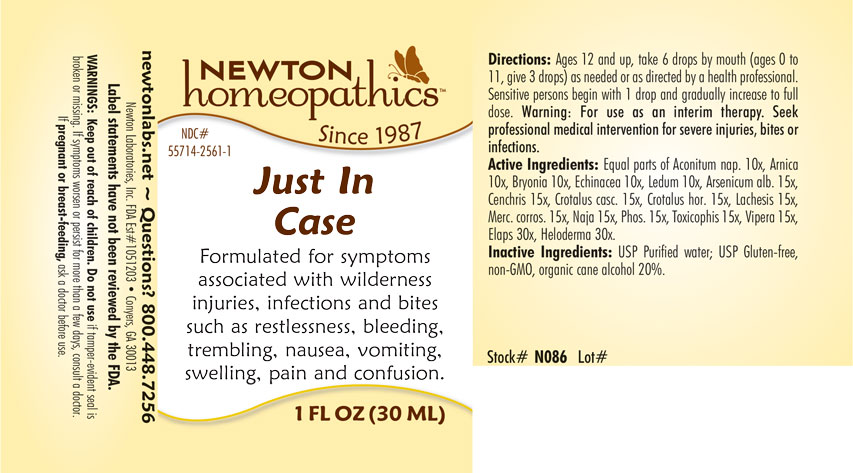 DRUG LABEL: Just In Case
NDC: 55714-2561 | Form: LIQUID
Manufacturer: Newton Laboratories, Inc.
Category: homeopathic | Type: HUMAN OTC DRUG LABEL
Date: 20250210

ACTIVE INGREDIENTS: BRYONIA ALBA ROOT 10 [hp_X]/1 mL; ECHINACEA, UNSPECIFIED 10 [hp_X]/1 mL; RHODODENDRON TOMENTOSUM LEAFY TWIG 10 [hp_X]/1 mL; ARSENIC TRIOXIDE 15 [hp_X]/1 mL; AGKISTRODON CONTORTRIX VENOM 15 [hp_X]/1 mL; CROTALUS DURISSUS TERRIFICUS VENOM 15 [hp_X]/1 mL; CROTALUS HORRIDUS HORRIDUS VENOM 15 [hp_X]/1 mL; ACONITUM NAPELLUS 10 [hp_X]/1 mL; MERCURIC CHLORIDE 15 [hp_X]/1 mL; NAJA NAJA VENOM 15 [hp_X]/1 mL; PHOSPHORUS 15 [hp_X]/1 mL; AGKISTRODON PISCIVORUS VENOM 15 [hp_X]/1 mL; VIPERA BERUS VENOM 15 [hp_X]/1 mL; MICRURUS CORALLINUS VENOM 30 [hp_X]/1 mL; HELODERMA HORRIDUM VENOM 30 [hp_X]/1 mL; ARNICA MONTANA 10 [hp_X]/1 mL; LACHESIS MUTA VENOM 15 [hp_X]/1 mL
INACTIVE INGREDIENTS: WATER; ALCOHOL

Just 2561L

INDICATIONS & USAGE SECTION

Formulated for symptoms associated with wilderness injuries, infections and bites such as restlessness, bleeding, trembling, nausea, vomiting, swelling, pain and confusion.

DOSAGE & ADMINISTRATION SECTION

Directions: Ages 12 and up, take 6 drops by mouth (ages 0 to 11, give 3 drops) as needed or as directed by a health professional. Sensitive persons begin with 1 drop and gradually increase to full dose. Warning: For use as an interim therapy. Seek professional medical intervention for severe injuries, bites or infections.

OTC - ACTIVE INGREDIENT SECTION

Equal parts of Aconitum napellus 10x, Arnica montana 10x, Bryonia 10x, Echinacea 10x, Ledum palustre 10x, Arsenicum album 15x, Cenchris contortrix 15x, Crotalus cascavella 15x, Crotalus horridus 15x, Lachesis mutus 15x, Mercurius corrosivus 15x, Naja tripudians 15x, Phosphorus 15x, Toxicophis pugnax 15x, Vipera berus 15x, Elaps corallinus 30x, Heloderma 30x.

OTC - PURPOSE SECTION

Formulated for symptoms associated with wilderness injuries, infections and bites such as restlessness, bleeding, trembling, nausea, vomiting, swelling, pain and confusion.

INACTIVE INGREDIENT SECTION

Inactive Ingredients: USP Purified Water; USP Gluten-free, non-GMO, organic cane alcohol 20%.

QUESTIONS SECTION

newtonlabs.net – Questions? 800.448.7256

Newton Laboratories, Inc. FDA Est # 1051203 - Conyers, GA 30013

WARNINGS SECTION

WARNINGS: Keep out of reach of children. Do not use if tamper-evident seal is broken or missing. If symptoms worsen or persist for more than a few days, consult a doctor. If pregnant or breast-feeding, ask a doctor before use.

OTC - PREGNANCY OR BREAST FEEDING SECTION

If pregnant or breast-feeding, ask a doctor before use.

OTC - KEEP OUT OF REACH OF CHILDREN SECTION

Keep out of reach of children.